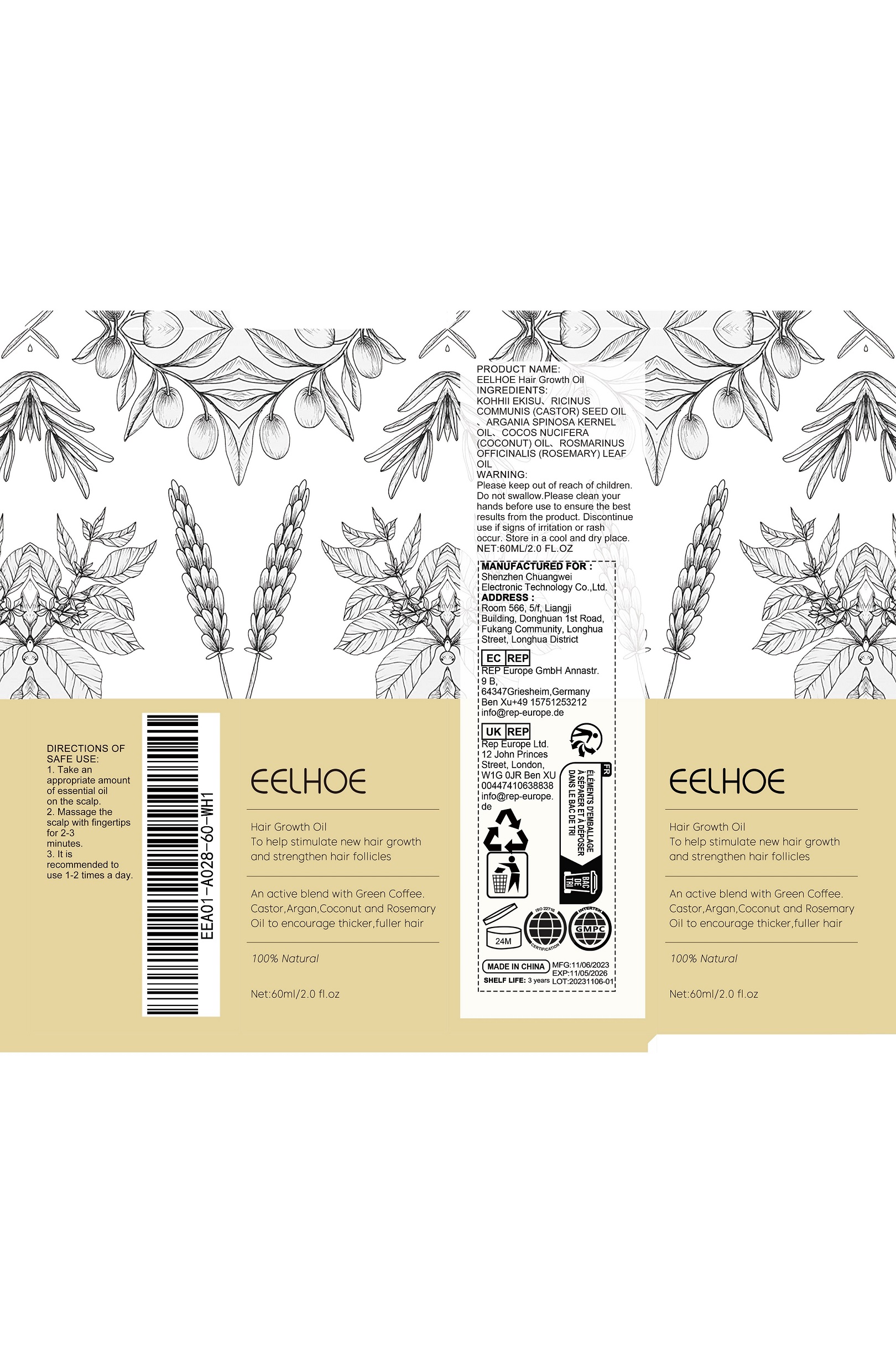 DRUG LABEL: EELHOE Hair Growth
NDC: 84718-001 | Form: OIL
Manufacturer: Shenzhen Chuangwei Electronic Technology Co., Ltd.
Category: otc | Type: HUMAN OTC DRUG LABEL
Date: 20240927

ACTIVE INGREDIENTS: CASTOR OIL 600 g/1000 g; ARGAN OIL 80 g/1000 g; COCONUT OIL 300 g/1000 g; ROSEMARY OIL 10 g/1000 g; ARABICA COFFEE BEAN 10 g/1000 g

Ingredient

KOHHII EKISU、RICINUSCOMMUNIS(CASTOR)SEED OILARGANIA SPINOSA KERNELOIL、COCOS NUCIFERA(COCONUT)OIL、ROSMARINUSOFFICINALIS (ROSEMARY)LEAFOIL

Warnings

Please keep out of reach of children.Do not swallow.Please clean yourhands before use to ensure the bestresults from the product. Discontinueuse if signs of irritation or rashoccur. Store in a cool and dry place.

INACTIVE INGREDIENT

none

DOSAGE AND ADMINISTRATION

none

INDICATIONS AND USAGE

none

KEEP OUT OF REACH OF CHILDREN

none

PURPOSE

e